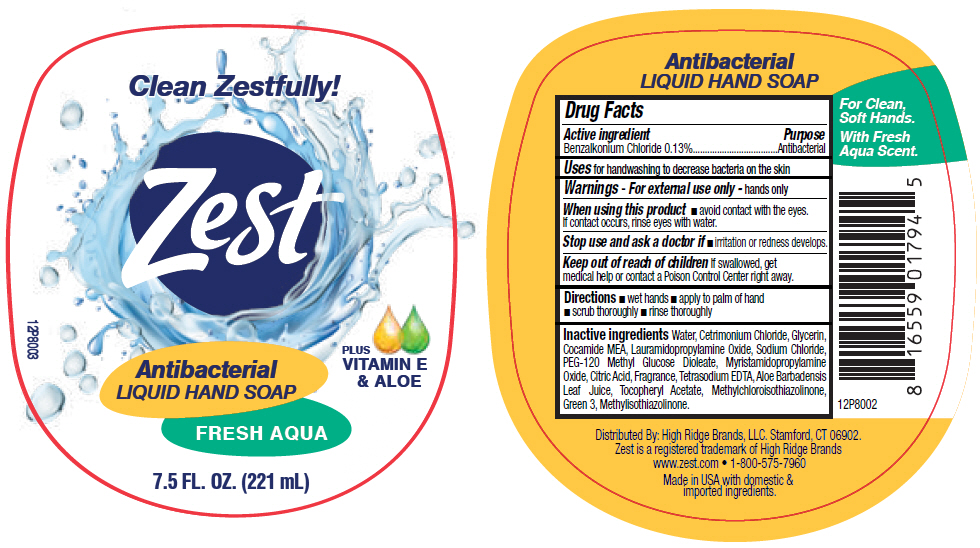 DRUG LABEL: Zest Aqua Antibacterial Hand
NDC: 81277-179 | Form: SOAP
Manufacturer: TCP HRB Holdings
Category: otc | Type: HUMAN OTC DRUG LABEL
Date: 20240301

ACTIVE INGREDIENTS: BENZALKONIUM CHLORIDE 13 mg/10 mL
INACTIVE INGREDIENTS: WATER; CETRIMONIUM CHLORIDE; GLYCERIN; LAURAMIDOPROPYLAMINE OXIDE; COCO MONOETHANOLAMIDE; SODIUM CHLORIDE; PEG-120 METHYL GLUCOSE DIOLEATE; CITRIC ACID MONOHYDRATE; EDETATE SODIUM; METHYLCHLOROISOTHIAZOLINONE; METHYLISOTHIAZOLINONE; FD&C GREEN NO. 3; ALOE VERA LEAF; .ALPHA.-TOCOPHEROL ACETATE

Zest Aqua Antibacterial Hand Soap

Drug Facts

Active ingredient

Benzalkonium Chloride 0.13%

Purpose

Antibacterial

INDICATIONS AND USAGE

Uses for handwashing to decrease bacteria on the skin

Warnings

For external use only - hands only

When using this product

- avoid contact with the eyes. If contact occurs, rinse eyes with water.

Stop use and ask a doctor if

- irritation or redness develops.

Keep out of reach of children If swallowed, get medical help or contact a Poison Control Center right away.

Directions

- wet hands
- apply to palm of hand
- scrub thoroughly
- rinse thoroughly

Inactive ingredients

Water, Cetrimonium Chloride, Glycerin, Cocamide MEA, Lauramidopropylamine Oxide, Sodium Chloride, PEG-120 Methyl Glucose Dioleate, Myristamidopropylamine Oxide, Citric Acid, Fragrance, Tetrasodium EDTA, Aloe Barbadensis Leaf Juice, Tocopheryl Acetate, Methylchloroisothiazolinone, Green 3, Methylisothiazolinone.

Distributed By: High Ridge Brands, LLC. Stamford, CT 06902.

PRINCIPAL DISPLAY PANEL - 221 mL Bottle Label

Clean Zestfully!

Zest

Antibacterial
LIQUID HAND SOAP

PLUS
VITAMIN E
& ALOE

FRESH AQUA

7.5 FL. OZ. (221 mL)

12P8003